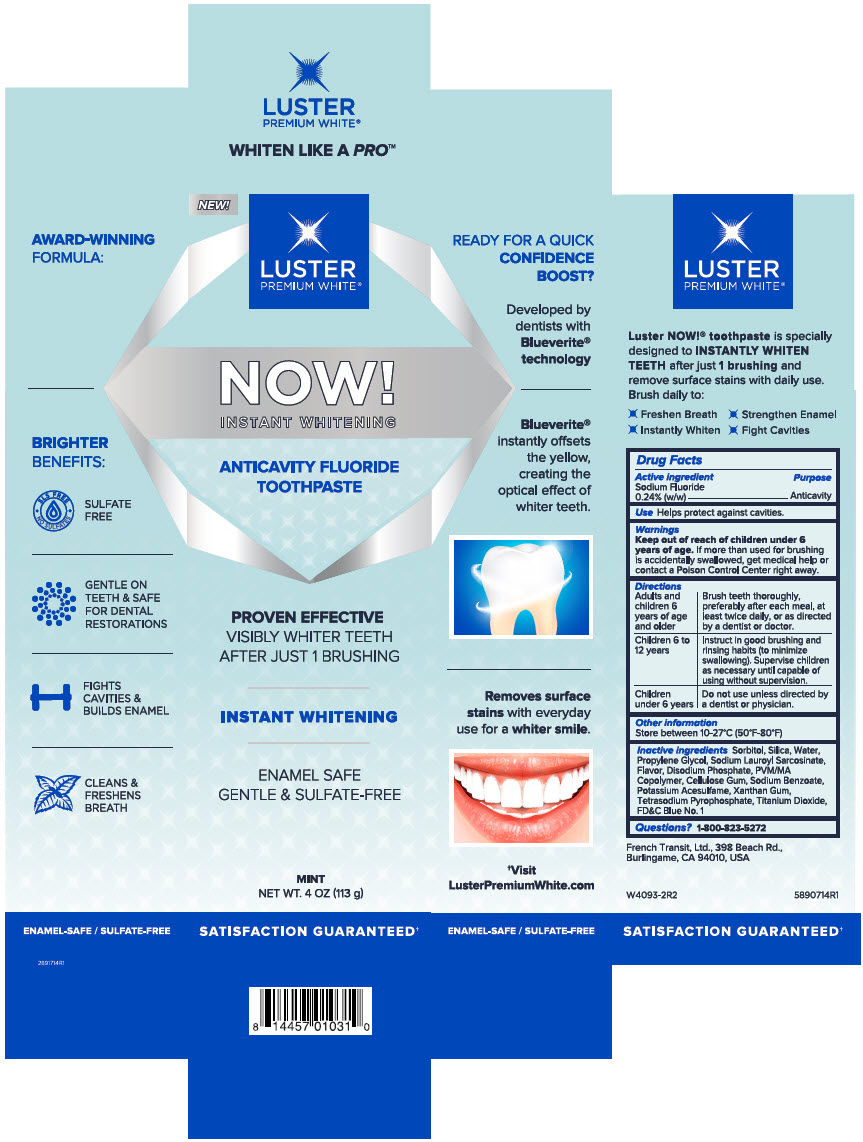 DRUG LABEL: Luster Premium White 
NDC: 72805-130 | Form: PASTE
Manufacturer: French Transit, Ltd.
Category: otc | Type: HUMAN OTC DRUG LABEL
Date: 20220112

ACTIVE INGREDIENTS: Sodium Fluoride 0.24 g/100 g
INACTIVE INGREDIENTS: Sorbitol; Silicon Dioxide; Water; Propylene Glycol; Sodium Lauroyl Sarcosinate; FD&C Blue No. 1; Sodium Phosphate, Dibasic, Anhydrous; Carboxymethylcellulose Sodium, Unspecified; Sodium Benzoate; Acesulfame Potassium; Titanium Dioxide; Xanthan Gum; Sodium Pyrophosphate

Luster Premium White®
Now!

Drug Facts

Active ingredient

Sodium Fluoride 0.24% (w/w)

Purpose

Anticavity

Use

Helps protect against cavities.

Warnings

Keep out of reach of children under 6 years of age. If more than used for brushing is accidentally swallowed, get medical help or contact a Poison Control Center right away.

Directions

Adults and children 6 years of age and older | Brush teeth thoroughly, preferably after each meal, at least twice daily, or as directed by a dentist or doctor.
Children 6 to 12 years | Instruct in good brushing and rinsing habits (to minimize swallowing). Supervise children as necessary until capable of using without supervision.
Children under 6 years | Do not use unless directed by a dentist or physician.

Other information

Store between 10-27°C (50°F-80°F)

Inactive ingredients

Sorbitol, Silica, Water, Propylene Glycol, Sodium Lauroyl Sarcosinate, Flavor, Disodium Phosphate, PVM/MA Copolymer, Cellulose Gum, Sodium Benzoate, Potassium Acesulfame, Xanthan Gum, Tetrasodium Pyrophosphate, Titanium Dioxide, FD&C Blue No. 1

Questions?

1-800-823-5272

PRINCIPAL DISPLAY PANEL - 113 g Tube Box

NEW!

LUSTER
PREMIUM WHITE®

NOW!
INSTANT WHITENING

ANTICAVITY FLUORIDE
TOOTHPASTE

PROVEN EFFECTIVE
VISIBLY WHITER TEETH
AFTER JUST 1 BRUSHING

INSTANT WHITENING

ENAMEL SAFE
GENTLE & SULFATE-FREE

MINT
NET WT. 4 OZ (113 g)

SATISFACTION GUARANTEED†